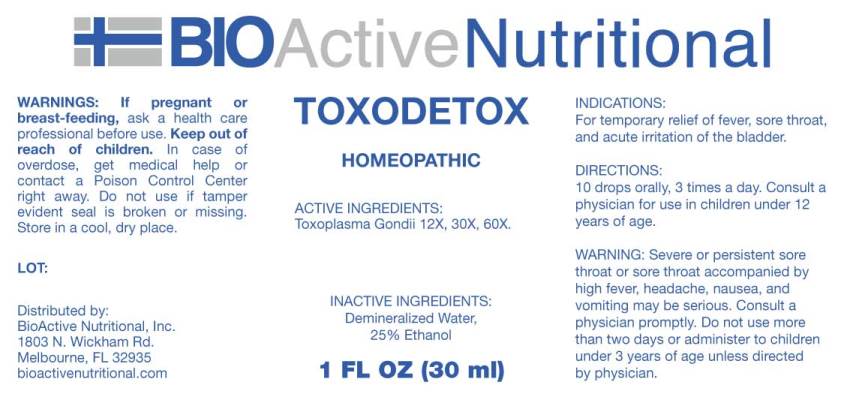 DRUG LABEL: Toxodetox
NDC: 43857-0312 | Form: LIQUID
Manufacturer: BioActive Nutritional, Inc.
Category: homeopathic | Type: HUMAN OTC DRUG LABEL
Date: 20180625

ACTIVE INGREDIENTS: TOXOPLASMA GONDII 12 [hp_X]/1 mL
INACTIVE INGREDIENTS: WATER; ALCOHOL

Drug Facts:

ACTIVE INGREDIENTS:

Toxoplasma Gondii 12X, 30X, 60X.

INDICATIONS:

For temporary relief of fever, sore throat, and acute irritation of the bladder.

WARNINGS:

If pregnant or breast-feeding, ask a health care professional before use.

Keep out of reach of children. In case of overdose, get medical help or contact a Poison Control Center right away.

Do not use if tamper evident seal is broken or missing.

Store in cool, dry place.

Warning: Severe or persistent sore throat or sore throat accompanied by high fever, headache, nausea, and vomiting may be serious. Consult a physician promptly. Do not use more than two days or administer to children under 3 years of age unless directed by a physician.

Keep out of reach of children. In case of overdose, get medical help or contact a Poison Control Center right away.

DIRECTIONS:

10 drops orally, 3 times a day. Consult a physician for use in children under 12 years of age.

INDICATIONS:

For temporary relief of fever, sore throat, and acute irritation of the bladder.

INACTIVE INGREDIENTS:

Demineralized Water, 25% Ethanol

QUESTIONS:

Distributed by:

BioActive Nutritional, Inc.

1803 N. Wickham Rd.

Melbourne, FL 32935

bioactivenutritional.com

PACKAGE LABEL DISPLAY:

BIOActive Nutritional
TOXODETOX
HOMEOPATHIC
1 FL OZ (30 ml)